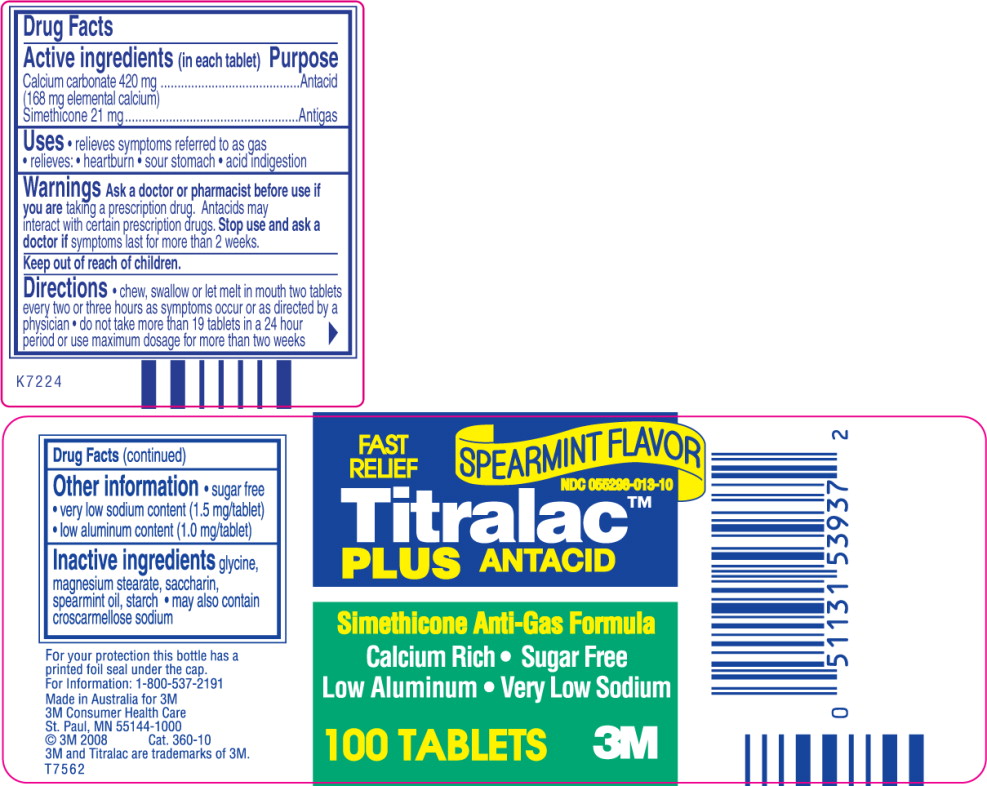 DRUG LABEL: Titralac Plus
NDC: 55298-013 | Form: TABLET
Manufacturer: iNova Pharmaceuticals Pty, Ltd
Category: otc | Type: HUMAN OTC DRUG LABEL
Date: 20110501

ACTIVE INGREDIENTS: Calcium Carbonate 420 mg/1 1; dimethicone 21 mg/1 1
INACTIVE INGREDIENTS: glycine; magnesium stearate; saccharin; spearmint oil; starch, corn

Active ingredients

(in each tablet)

Calcium carbonate 420 mg

(168 mg elemental calcium)

Simethicone 21 mg

Purpose

Antacid

Antigas

Uses

- relieves symptoms referred to as gas
- relieves:
  - heartburn
  - sour stomach
  - acid indigestion

Warnings

Ask a doctor or pharmacist before use if you are taking a prescription drug. Antacids may interact with certain prescription drugs.

Stop use and ask a doctor if symptoms last for more than 2 weeks.

Directions

- chew, swallow or let melt in mouth two tablets every two or three hours as symptoms occur or as directed by a physician
- do not take more than 19 tablets in a 24 hour period or use maximum dosage for more than two weeks

Other information

- sugar free
- very low sodium content (1.5 mg/tablet)
- low aluminum content (1.0 mg/tablet)

Inactive ingredients

glycine, magnesium stearate, saccharin, spearmint oil, starch

- may also contain croscarmellose sodium

For your protection this bottle has a printed foil seal under the cap.

For Information: 1-800-537-2191

Made in Australia for 3M

3M Consumer Health Care

St. Paul, MN 55144-1000

© 3M 2008 Cat. 360-10

3M and Titralac are trademarks of 3M.

T7562

Principal Display Panel – Bottle Label

SPEARMINT FLAVOR

NDC 055298-013-10

FAST RELIEF

Titralac™

PLUS ANTACID

Simethicone Anti-Gas Formula

Calcium Rich • Sugar Free

Low Aluminum • Very Low Sodium

100 TABLETS 3M